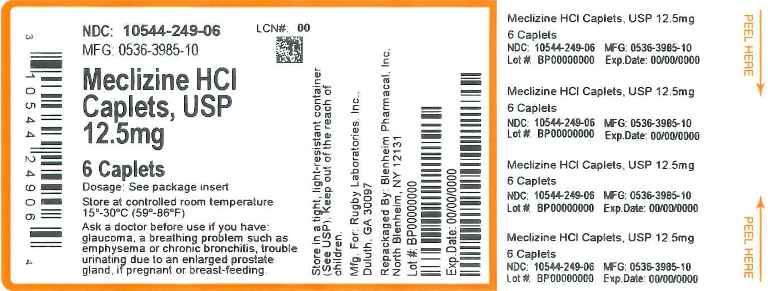 DRUG LABEL: Meclizine HCl
NDC: 10544-249 | Form: TABLET
Manufacturer: Blenheim Pharmacal, Inc.
Category: otc | Type: HUMAN OTC DRUG LABEL
Date: 20150318

ACTIVE INGREDIENTS: MECLIZINE HYDROCHLORIDE 12.5 mg/1 1
INACTIVE INGREDIENTS: CROSCARMELLOSE SODIUM; ANHYDROUS DIBASIC CALCIUM PHOSPHATE; MAGNESIUM STEARATE; CELLULOSE, MICROCRYSTALLINE; STEARIC ACID; SILICON DIOXIDE

Meclizine HCl Caplets USP

Active Ingredient

(in each caplet)

Meclizine HCl 12.5 mg USP

Purpose

Antiemetic

Uses

prevents and treats nausea, vomiting, or dizziness due to motion sickness

WARNINGS

Ask a doctor before use if you have

- glaucoma
- a breathing problem such as emphysema or chronic bronchitis
- trouble urinating due to an enlarged prostate gland

Ask a doctor or pharmacist before use if you are taking sedatives or tranquilizers

When using this product

- you may get drowsy
- avoid alcoholic drinks
- alcohol, sedatives & tranquilizers may increase drowsiness
- be careful when driving a motor vehicle or operating a machinery
  If pregnant or breast-feeding, ask a health professional before use.
  Keep out of reach of children. In case of overdose, get medical help or contact a Poison Control Center right away.

Directions

- adults and children 12 years and over: 2-4 caplets once daily
- children under 12 years: ask a doctor

Other Information

- each caplet contains: calcium 51 mg
- store at room temperature 15°-30°C (59°-86°F)

Inactive Ingredients

croscarmellose sodium, dicalcium phosphate, magnesium stearate, microcrystalline cellulose, silicon dioxide, stearic acid

Questions or Comments

Call 1-800-645-2158, 9 am – 5 pm ET, Monday - Friday

TAMPER EVIDENT: DO NOT USE IF CARTON IS OPENED OR BLISTER UNIT IS BROKEN OR DAMAGED

Rugby® Duluth, Georgia 30097

Principal Display Panel

Meclizine HCl Caplets, USP 12.5mg

6 Caplets

NDC 10544-249-06